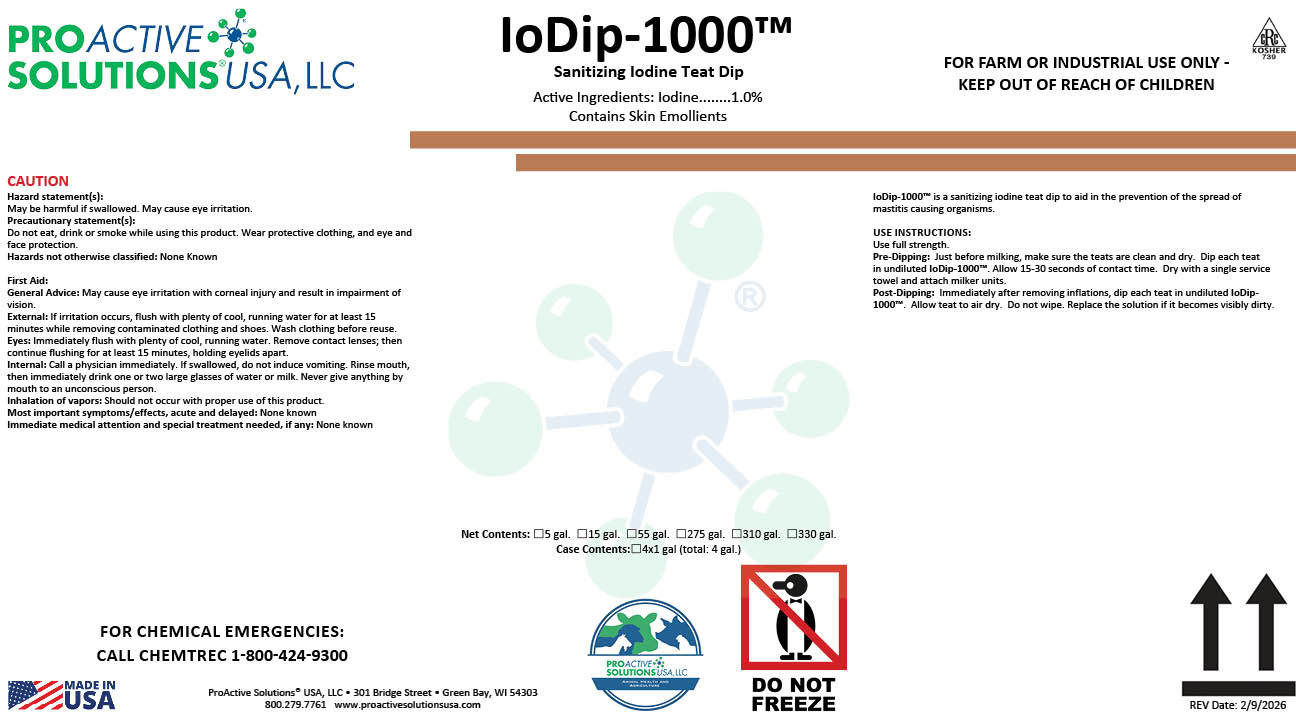 DRUG LABEL: IoDip 1000
NDC: 63927-4215 | Form: LIQUID
Manufacturer: ProActive Solutions USA, LLC
Category: animal | Type: OTC ANIMAL DRUG LABEL
Date: 20260210

ACTIVE INGREDIENTS: IODINE 1 kg/100 kg

IoDip 1000

Iodip 1000

IoDip-1000™ is a sanitizing iodine teat dip to aid in the prevention of the spread of
mastitis causing organisms.
USE INSTRUCTIONS:
Use full strength.
Pre-Dipping: Just before milking, make sure the teats are clean and dry. Dip each teat
in undiluted IoDip-1000™. Allow 15-30 seconds of contact time. Dry with a single service
towel and attach milker units.
Post-Dipping: Immediately after removing inflations, dip each teat in undiluted IoDip-
1000™. Allow teat to air dry. Do not wipe. Replace the solution if it becomes visibly dirty.

Hazard statement(s):
May be harmful if swallowed. May cause eye irritation.
Precautionary statement(s):
Do not eat, drink or smoke while using this product. Wear protective clothing, and eye and
face protection.
Hazards not otherwise classified: None Known
First Aid:
General Advice: May cause eye irritation with corneal injury and result in impairment of
vision.
External: If irritation occurs, flush with plenty of cool, running water for at least 15
minutes while removing contaminated clothing and shoes. Wash clothing before reuse.
Eyes: Immediately flush with plenty of cool, running water. Remove contact lenses; then
continue flushing for at least 15 minutes, holding eyelids apart.
Internal: Call a physician immediately. If swallowed, do not induce vomiting. Rinse mouth,
then immediately drink one or two large glasses of water or milk. Never give anything by
mouth to an unconscious person.
Inhalation of vapors: Should not occur with proper use of this product.
Most important symptoms/effects, acute and delayed: None known
Immediate medical attention and special treatment needed, if any: None known